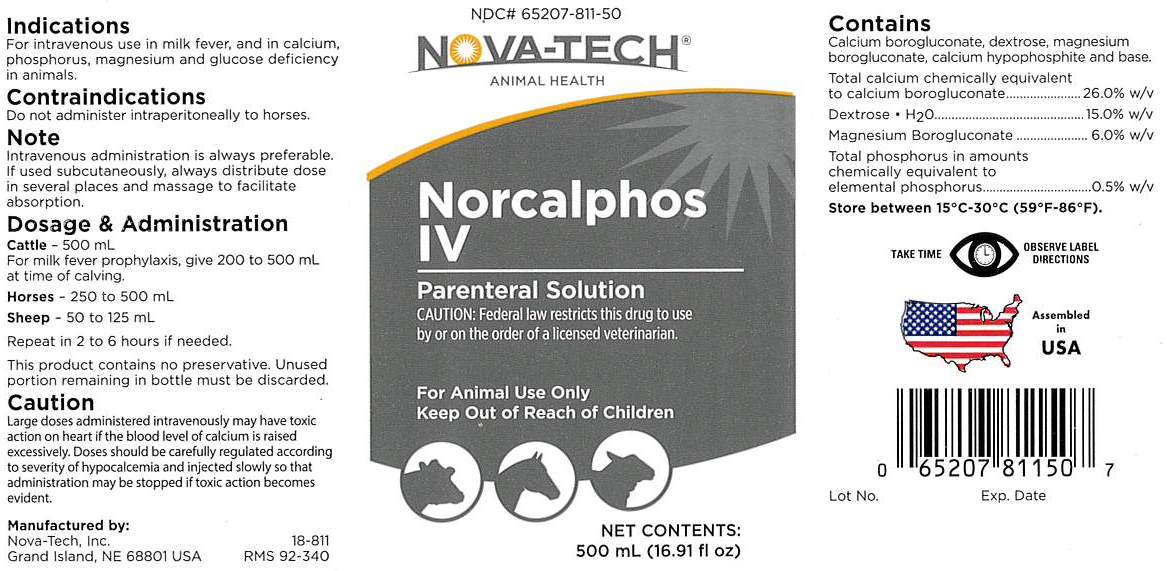 DRUG LABEL: Norcalphos
NDC: 65207-811 | Form: INJECTION, SOLUTION
Manufacturer: Nova-Tech, Inc.
Category: animal | Type: PRESCRIPTION ANIMAL DRUG LABEL
Date: 20230208

ACTIVE INGREDIENTS: Calcium Borogluconate 26 g/100 mL; DEXTROSE MONOHYDRATE 15 g/100 mL; MAGNESIUM GLUCONATE 6 g/100 mL; Phosphorus 0.5 g/100 mL

Norcalphos IV

VETERINARY INDICATIONS

Parenteral Solution

FOR ANIMAL USE ONLY

Contraindications

Do not administer intraperitoneally to horses.

Indications

For intravenous use in milk fever, and in calcium, phosphorus, magnesium and glucose deficiency in animals.

Note

Intravenous administration is always preferable. If used subcutaneously, always distribute dose in several places and massage to facilitate absorption.

Dosage & Administration

Cattle - 500 mL.

For milk fever prophylaxis, give 200-500 mL at time of calving.

Horses - 250-500 mL

Sheep - 50-125 mL

Repeat in 2 to 6 hours if needed.

This product contains no preservative. Unused portion remaining in bottle must be discarded.

Caution

Large doses administered intravenously may have toxic action on heart if the blood level of calcium is raised excessively. Doses should be carefully regulated according to severitity of hypocalcemia and injected slowly so that administration may be stopped if toxic action becomes evident.

KEEP OUT OF REACH OF CHILDREN

CAUTION:

Federal law restricts this drug to use by or on the order of a licensed veterinarian.

CONTAINS

Calcium borogluconate, dextrose, magnesium borogluconate, calcium hypophosphite and base.

Total calcium chemically equivalent to calcium borogluconate .......................................... 26.0% w/v

Dextrose • H2O ......................................................................................................... 15.0% w/v

Magnesium Borogluconate ............................................................................................ 6.0% w/v

Total phosphorus in amounts chemically equivalent to elemental phosphorus ...................... 0.5% w/v

STORAGE AND HANDLING

Store between 15°C-30°C (59°F-86°F).

PRECAUTIONS

TAKE TIME OBSERVE LABEL DIRECTIONS

INFORMATION FOR OWNERS/CAREGIVERS

Manufactured by:

Nova-Tech, Inc.

Grand Island, NE 68801 USA

18-811

RMS 92-340

NDC# 65207-811-50

Net Contents:

500 mL (16.91 fl oz)

Assembled in USA

Lot No.

Exp. Date